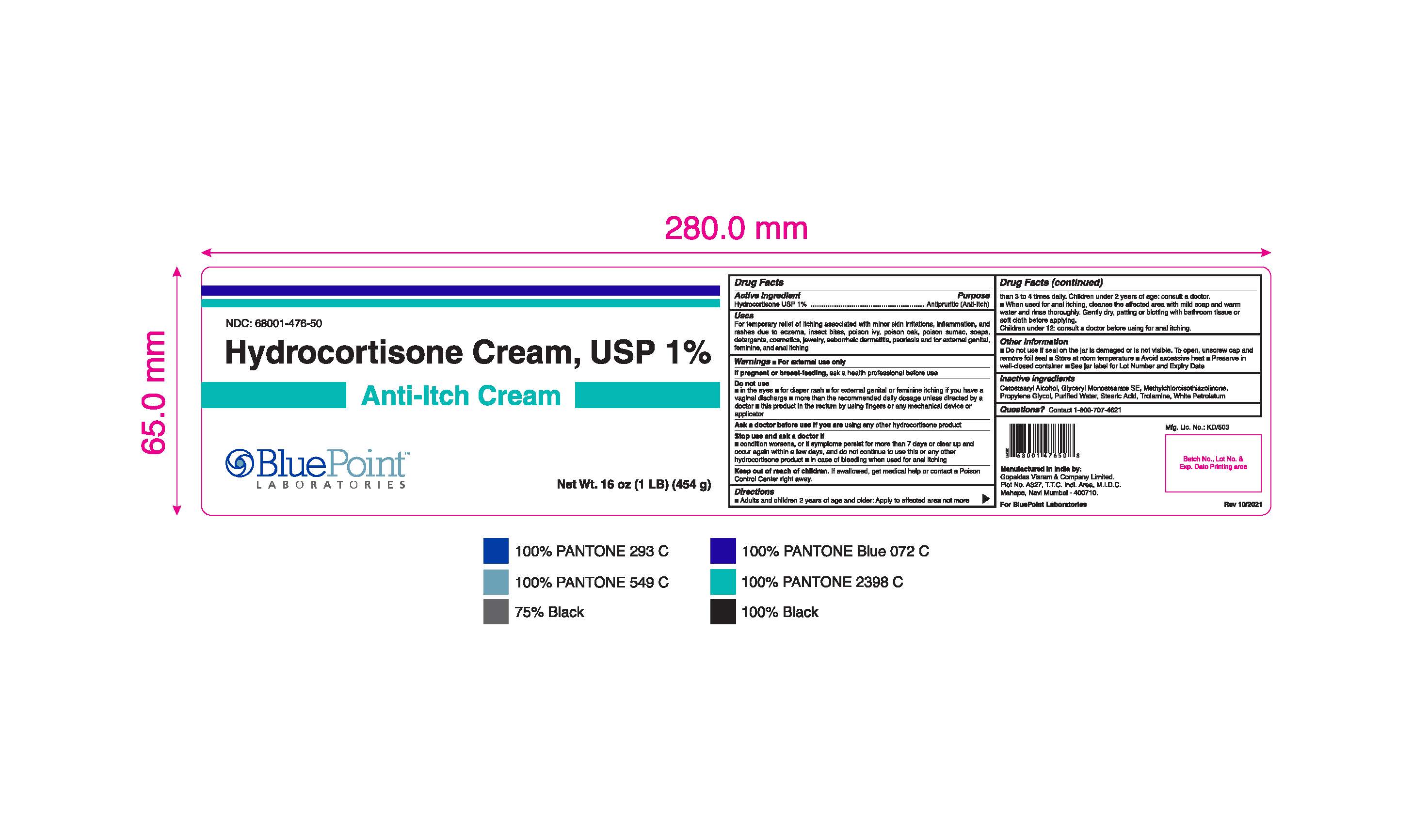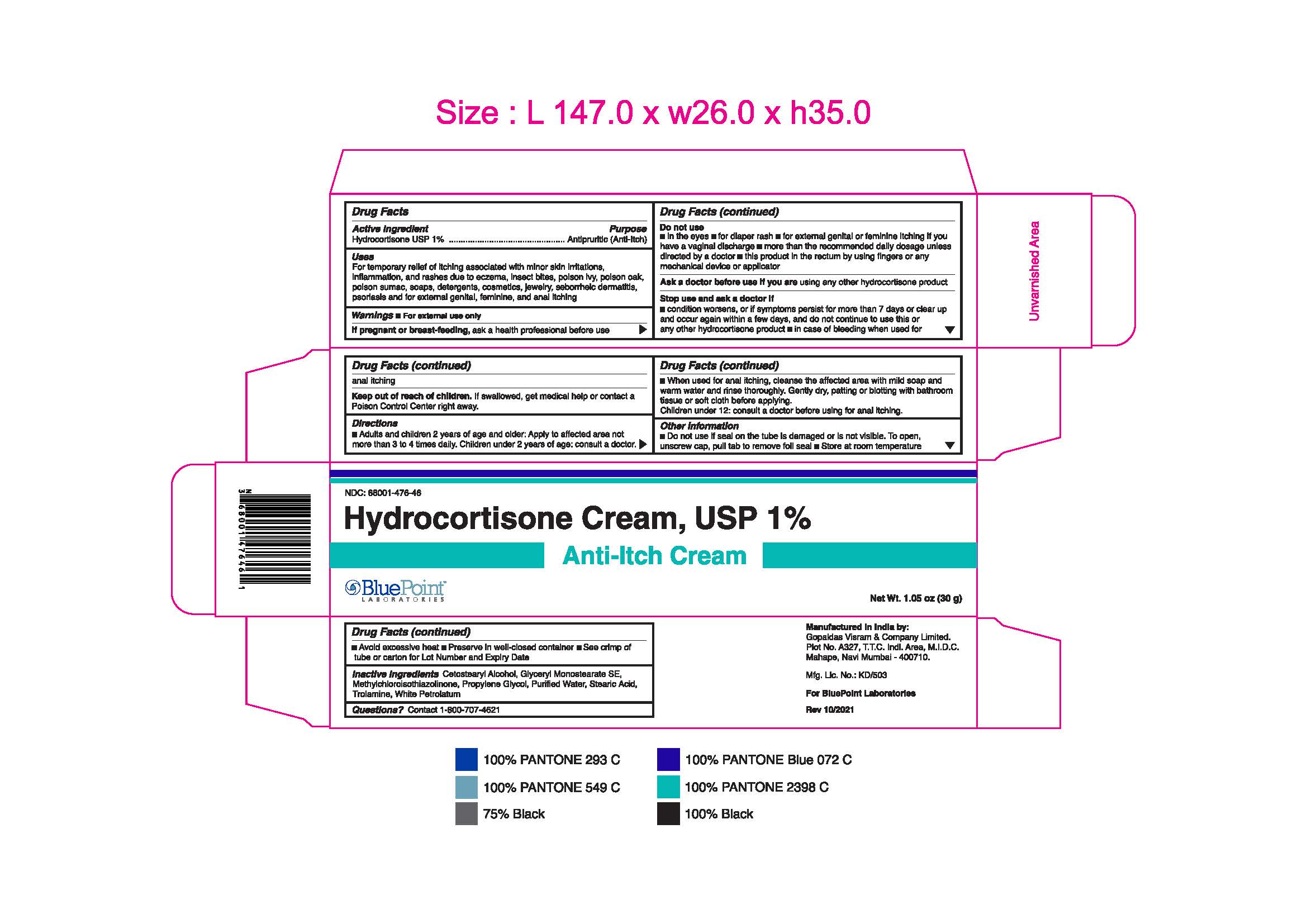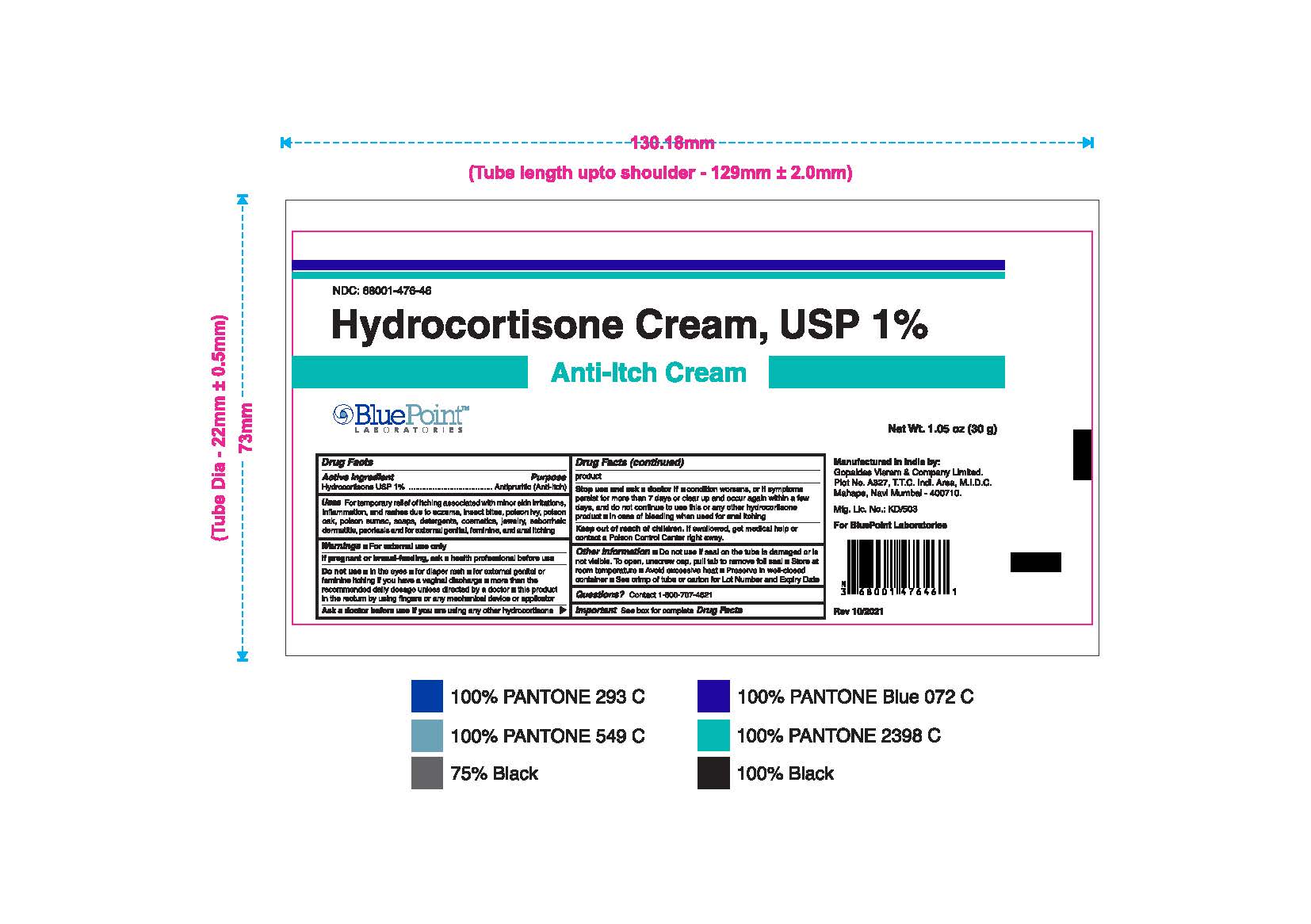 DRUG LABEL: Hydrocortisone
NDC: 68001-476 | Form: CREAM
Manufacturer: BluePoint Laboratories
Category: otc | Type: HUMAN OTC DRUG LABEL
Date: 20231117

ACTIVE INGREDIENTS: HYDROCORTISONE 1 g/100 g
INACTIVE INGREDIENTS: WHITE PETROLATUM; STEARIC ACID; TROLAMINE; PROPYLENE GLYCOL; WATER; CETOSTEARYL ALCOHOL; GLYCERYL STEARATE SE; METHYLCHLOROISOTHIAZOLINONE

Hydrocortisone 1% Cream

Active Ingredient

Hydrocortisone USP 1%

Purpose

Antipruritic (Anti-Itch)

Uses

For temporary relief of itching associated with minor skin irritations, inflammation, and rashes due to eczema, insect bites, poison ivy, poison oak, poison sumac, soaps, detergents, cosmetics, jewelry, seborrheic dermatitis, psoriasis, and for external genital, feminine, and anal itching.

Warnings

For external use only

If pregnant or breast-feeding,

ask a health professional before use

Do not use

- in the eyes
- for diaper rash
- for external genital or feminine itching if you have a vaginal discharge
- more than the recommended daily dosage unless directed by a doctor
- this product in the rectum by using fingers or any mechanical device or applicator

Ask a doctor before use if you are using any other hydrocortisone product

Stop use and ask a doctor if

- Condition worsens, or if symptoms persist for more than 7 days or clear up and occur again within a few days, and do not continue to use this or any other hydrocortisone product
- in case of bleeding when used for anal itching

Keep out of reach of children

If swallowed, get medical help or contact a Poison Control Center right away.

Directions

- Adults and children 2 years of age and older: Apply to affected area not more than 3 to 4 times daily. Children under 2 years of age: consult a doctor.
- When used for anal itching, cleanse the affected area with mild soap and warm water and rinse thoroughly. Gently dry, patting or blotting with bathroom tissue or soft cloth before applying.
- Children under 12: consult a doctor before using for anal itching.

Other Information

- Do not use if seal on the tube is damaged or is not visible. To open, unscrew cap, pull tab to remove foil seal
- Store at room temperature
- Avoid excessive heat
- Preserve in well-closed container
- See crimp of tube or carton for Lot Number and Expiry Date

Inactive Ingredients

Cetostearyl Alcohol, Glyceryl Monostearate SE, Methylchloroisothiazolinone, Propylene Glycol, Purified Water, Stearic Acid, Trolamine, White Petrolatum

Questions?

Contact 1-800-707-4621

Manufactured in India by:

Gopaldas Visram & Company Limited

Plot No. A327, T.T.C Indl. Area, M.L.D.C

Mahape, Navi Mumbai - 400710.

Mfg. Lic. No.: KD/503

For BluePoint Laboratories

Rev 10/2021

Label

Hydrocortisone Cream, USP 1%

PACKAGE LABEL

Hydrocortisone Cream, USP 1%

PACKAGE LABEL

Hydrocortisone Cream, USP 1% Jar